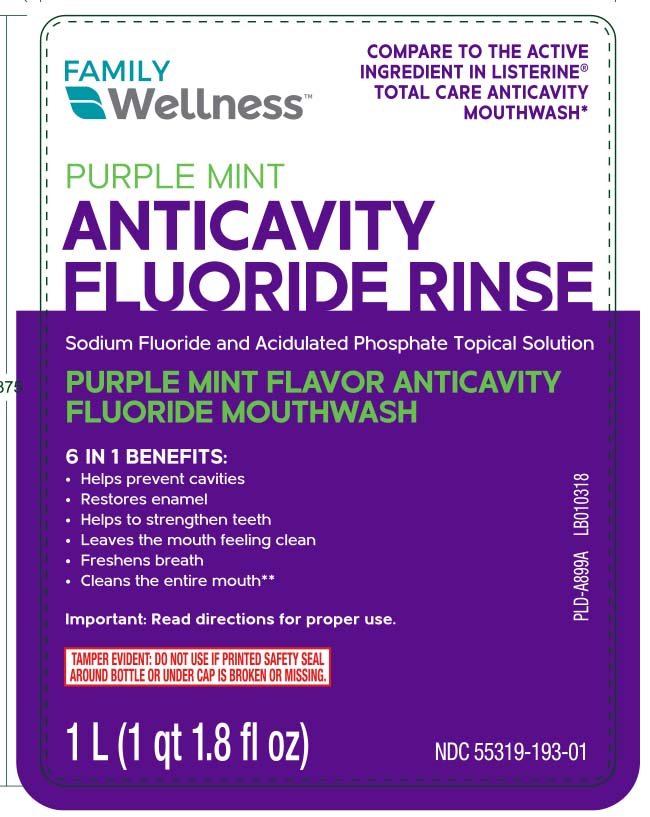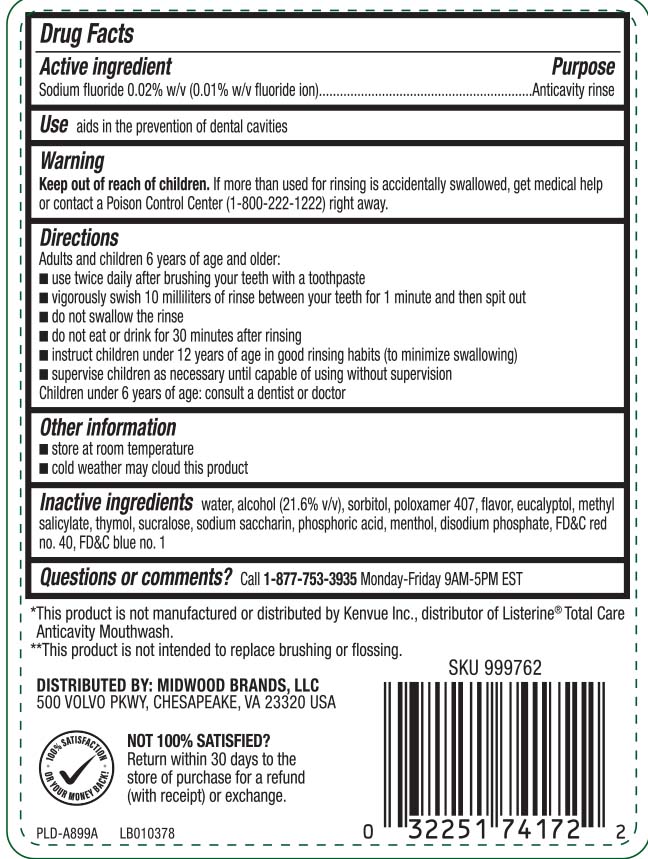 DRUG LABEL: Anticavity Fluoride
NDC: 55319-193 | Form: LIQUID
Manufacturer: Family Dollar (FAMILY WELLNESS)
Category: otc | Type: HUMAN OTC DRUG LABEL
Date: 20250709

ACTIVE INGREDIENTS: SODIUM FLUORIDE .1 mg/1 mL
INACTIVE INGREDIENTS: WATER; ALCOHOL; SORBITOL; POLOXAMER 407; EUCALYPTOL; METHYL SALICYLATE; THYMOL; SUCRALOSE; SACCHARIN SODIUM; PHOSPHORIC ACID; MENTHOL; DISODIUM PHOSPHATE; FD&C RED NO. 40; FD&C BLUE NO. 1

Kalaya Breath Refresh Antiseptic Oral Rinse-updated label for NDC

Active ingredient

Sodium fluoride 0.02% w/v (0.01% w/v fluoride ion)

Purposes

Anticavity rinse

Uses

aids in the prevention of dental cavities

Warning

Keep out of reach of children

If more than used for rinsing is accidentally swallowed, get medical help or contact a Poison Control Center (1-800-222-1222) right away

Directions

adults and children 12 years of age and older:

- use twice daily after brushing your teeth with a toothpaste
- vigorously swish 10 milliliters of rinse between your teeth for 1 minute and then spit out
- do not swallow the rinse
- do not each or drink for 30 minutes after rinsing
- instruct children under 12 years of age in good rinsing habits (to minimize swallowing)
- supervise children as necessary until capable of using without supervision

Children under 6 years of age: consult a dentist or doctor

Other information

- store at room temperature
- cold weather may cloud this product

Inactive ingredients

water, alcohol (21.6% v/v), sorbitol, poloxamer 407, flavor, eucalyptol, methyl salicylate, thymol, sucralose, sodium saccharin, phosphoric acid, menthol, disodium phosphate, FD&C red no. 40. FD&C blue no. 1

Questions or comments?

Call 1-877-753-3935 Monday-Friday 9AM-5PM EST

Principal display panel

*Compare to the active ingredients in Listerine® Total Care Anticavity Mouthwash

Purple Mint

Anticavity

Fluoride Rinse

Sodium Fluoride and Acidulated Phosphate Topical Solution

PURPLE MINT FLAVOR ANTICAVITY

FLUORIDE MOUTHWASH

6 IN 1 BENEFITS:

- Helps prevent cavities
- Restores enamel
- Helps to strengthen teeth
- Leaves the mouth feeling clean
- Freshens breath
- Cleans the entire mouth**

Important: Read directions for proper use.

L (qt fl oz)

*This product is not manufactured or distributed by Kenvue Inc., distributor of Listerine® Total Care Anticavity Mouthwash.

**This product is not intended to replace brushing or flossing.

TAMPER EVIDENT: DO NOT USE IF PRINTED SAFETY SEAL AROUND OR UNDER CAP IS BROKEN OR MISSING.

DISTRIBUTED BY: MIDWOOD BRANDS, LLC

500 VOLVO PKWY, CHESAPEAKE, VA 23320 USA

Package label

Anticavity Fluoride Rinse Purple Mint
Anticavity Fluoride Rinse Purple Mint